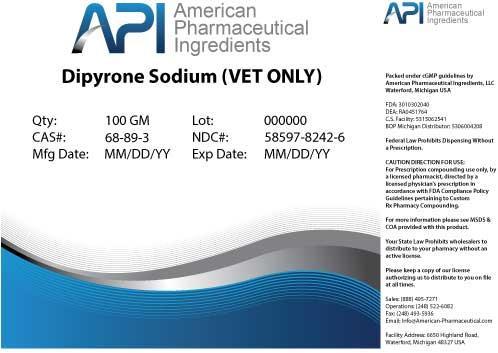 DRUG LABEL: METAMIZOLE SODIUM
NDC: 58597-8242 | Form: POWDER
Manufacturer: AMERICAN PHARMACEUTICAL INGREDIENTS LLC
Category: other | Type: BULK INGREDIENT
Date: 20140516

ACTIVE INGREDIENTS: METAMIZOLE SODIUM 1 g/1 g

METAMIZOLE SODIUM